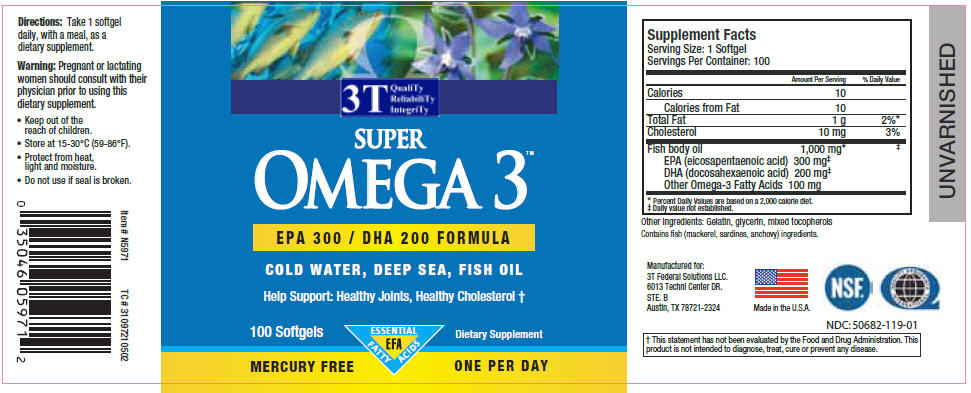 DRUG LABEL: Super Omega 3
NDC: 50682-119 | Form: CAPSULE, LIQUID FILLED
Manufacturer: 3T Federal Solutions LLC
Category: other | Type: DIETARY SUPPLEMENT
Date: 20120426

ACTIVE INGREDIENTS: Icosapent 300 mg/1 1; Doconexent 200 mg/1 1; Omega-3 Fatty Acids 100 mg/1 1
INACTIVE INGREDIENTS: Gelatin; glycerin; tocopherol; mackerel, unspecified; sardine, unspecified; anchovy, unspecified

Super Omega 3™

Supplement Facts

Dietary Supplement

Serving Size: 1 Softgel

Servings Per Container: 100

 | Amount Per Serving | % Daily Value
Calories | 10
Calories from Fat | 10
Total Fat | 1 g | 2% [Percent Daily Values are based on a 2,000 calorie diet.]
Cholesterol | 10 mg | 3%
Fish body oil EPA (eicosapentaenoic acid) 300 mg DHA (docosahexaenoic acid) 200 mg Other Omega-3 Fatty Acids 100 mg | 1,000 mg | [Daily value not established.]

Other ingredients: Gelatin, glycerin, mixed tocopherols

Contains fish (mackerel, sardines, anchovy) ingredients.

Directions

Take 1 softgel daily, with a meal, as a dietary supplement.

Warning

Pregnant or lactating women should consult with their physician prior to using this dietary supplement.

SAFE HANDLING WARNING

- Keep out of the reach of children.
- Store at 15-30°C (59-86°F).
- Protect from heat, light and moisture.
- Do not use if seal is broken.

Manufactured for:
3T Federal Solutions LLC.
6013 Techni Center DR.
STE. B
Austin, TX 78721-2324

HEALTH CLAIM

Help Support: Healthy Joints, Healthy Cholesterol

PRINCIPAL DISPLAY PANEL - 100 Capsule Bottle Label

3T
QualiTy
ReliabiliTy
IntegriTy

SUPER
OMEGA 3™

EPA 300 / DHA 200 FORMULA

COLD WATER, DEEP SEA, FISH OIL

Help Support: Healthy Joints, Healthy Cholesterol †

100 Softgels

ESSENTIAL
FATTY
ACIDS
EFA

Dietary Supplement

MERCURY FREE
ONE PER DAY